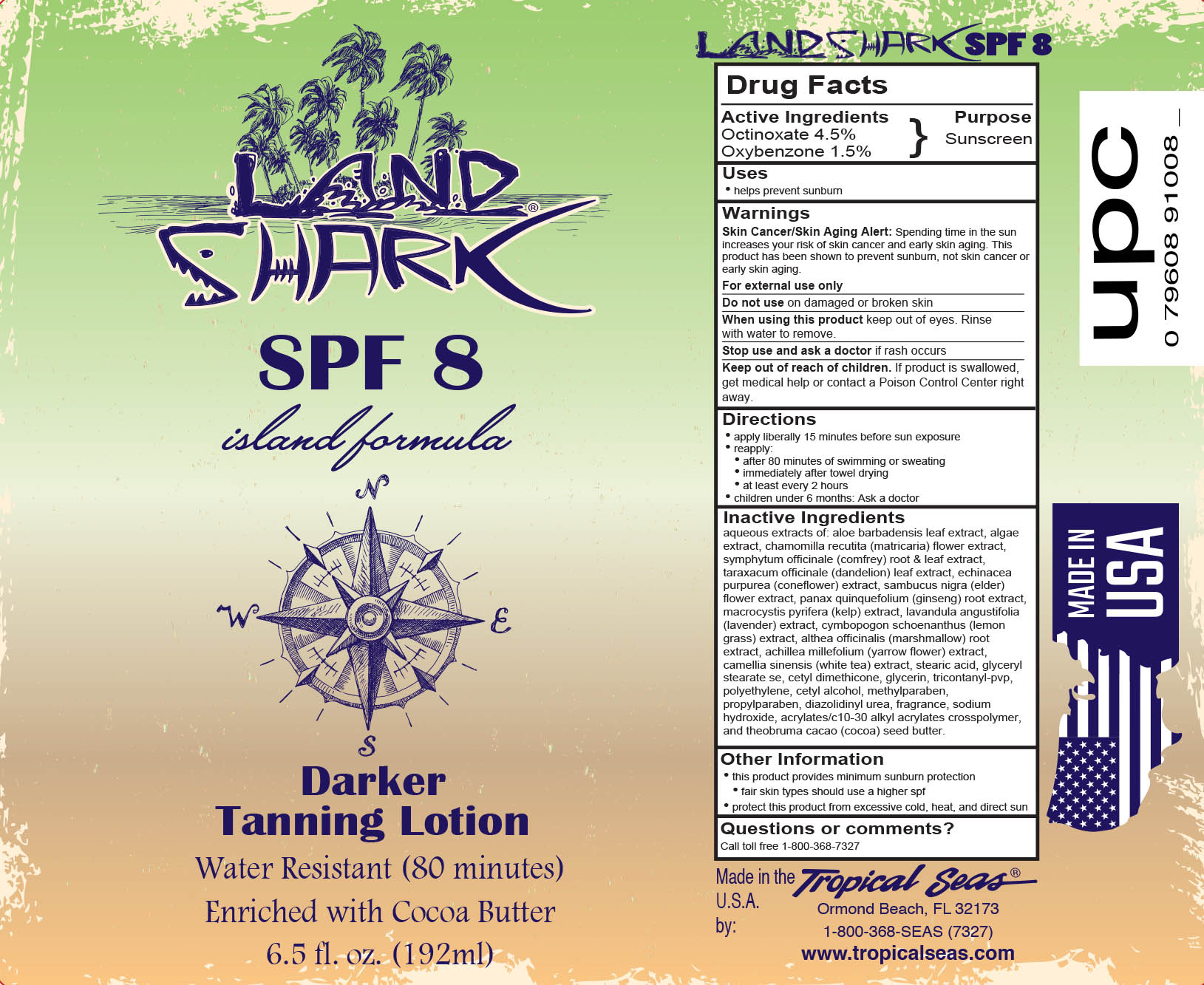 DRUG LABEL: Land Shark SPF 8
NDC: 52854-908 | Form: LOTION
Manufacturer: Tropical Seas, Inc.
Category: otc | Type: HUMAN OTC DRUG LABEL
Date: 20251104

ACTIVE INGREDIENTS: OCTINOXATE 4.5 g/100 mL; OXYBENZONE 1.5 g/100 mL
INACTIVE INGREDIENTS: CYMBOPOGON SCHOENANTHUS TOP; ALTHAEA OFFICINALIS ROOT; ACHILLEA MILLEFOLIUM FLOWER; GREEN TEA LEAF; STEARIC ACID; GLYCERYL STEARATE SE; TITANIUM DIOXIDE; CETYL DIMETHICONE 150; GLYCERIN; SODIUM HYDROXIDE; CETOSTEARYL ALCOHOL; POLYSORBATE 60; TRICONTANYL POVIDONE; HIGH DENSITY POLYETHYLENE; WATER; ALOE VERA LEAF; CARRAGEENAN; CHAMOMILE; SYMPHYTUM UPLANDICUM LEAF; COMFREY ROOT; TARAXACUM OFFICINALE LEAF; ECHINACEA, UNSPECIFIED; SAMBUCUS NIGRA FLOWER; AMERICAN GINSENG; MACROCYSTIS PYRIFERA; LAVANDULA ANGUSTIFOLIA FLOWERING TOP; CARBOMER COPOLYMER TYPE B (ALLYL PENTAERYTHRITOL CROSSLINKED); METHYLPARABEN; CETYL ALCOHOL; DIAZOLIDINYL UREA; PROPYLPARABEN; COCOA BUTTER

Drug Facts

Active Ingredients

Octinoxate 4.5%

Oxybenzone 1.5%

Purpose

Sunscreen

Uses

- helps prevent sunburn

Warnings

Skin Cancer/Skin Aging Alert: Spending time in the sun increases your risk of skin cancer and early skin aging. This product has been shown to prevent sunburn, not skin cancer or early skin aging.

For external use only

Do not use on damaged or broken skin

When using this product keep out of eyes. Rinse with water to remove.

Stop use and ask a doctor if rash occurs

Keep out of reach of children. If product is swallowed, get medical help or contact a Poison Control Center right away.

Directions

- apply liberally 15 minutes before sun exposure
- reapply:
  - after 80 minutes of swimming or sweating
  - immediately after towel drying
  - at least every 2 hours
- children under 6 months: Ask a doctor

Inactive Ingredients

aqueous extracts of: aloe barbadensis leaf extract, algae extract, chamomilla recutita (matricaria) flower extract, symphytum officinale (comfrey) root & leaf extract, taraxacum officinale (dandelion) leaf extract, echinacea purpurea (coneflower) extract, sambucus nigra (elder) flower extract, panax quinquefolium (ginseng) root extract, macrocystis pyrifera (kelp) extract, lavandula angustifolia (lavender) extract, cymbopogon schoenanthus (lemon grass) extract, althea officinalis (marshmallow) root extract, achillea millefolium (yarrow flower) extract, camellia sinensis (white tea) extract, stearic acid, glyceryl stearate se, cetyl dimethicone, glycerin, tricontanyl-pvp, polyethylene, cetyl alcohol, methylparaben, propylparaben, diazolidinyl urea, fragrance, sodium hydroxide, acrylates/c10-30 alkyl acrylates cross-polymer, and theobroma cacao (cocoa) seed butter.

Other Information

- protect this product from excessive heat and direct sun

Questions or comments?

Call toll free 1-800-368-7327

Principal Display Panel - Bottle Label

192 ml NDC: 52854-908-01